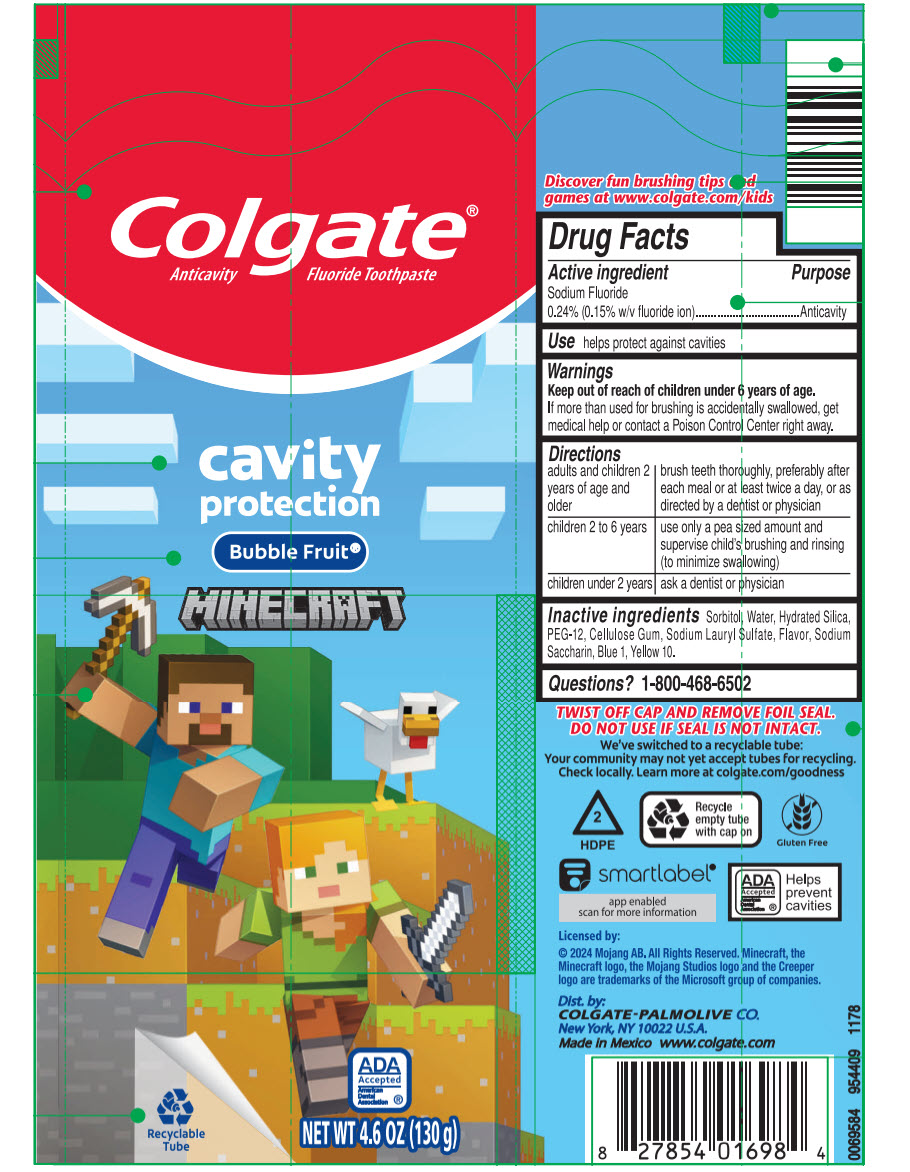 DRUG LABEL: Colgate Kids 
NDC: 65954-065 | Form: GEL, DENTIFRICE
Manufacturer: Mission Hills S.A de C.V
Category: otc | Type: HUMAN OTC DRUG LABEL
Date: 20260227

ACTIVE INGREDIENTS: SODIUM FLUORIDE 1.1 mg/1 g
INACTIVE INGREDIENTS: SORBITOL 476 mg/1 g; WATER; HYDRATED SILICA; POLYETHYLENE GLYCOL 600; CARBOXYMETHYLCELLULOSE SODIUM, UNSPECIFIED FORM; SODIUM LAURYL SULFATE; SACCHARIN SODIUM; TITANIUM DIOXIDE; FD&C BLUE NO. 1; D&C YELLOW NO. 10

Colgate® Kids Fluoride Toothpaste Mild Bubble Fruit® Flavor

Drug Facts

Active ingredient

Sodium fluoride 0.24% (0.15% w/v fluoride ion)

Purpose

Anticavity

Use

helps protect against cavities

Warnings

Keep out of reach of children under 6 years of age. If more than used for brushing is accidentally swallowed, get medical help or contact a Poison Control Center right away.

Directions

adults and children 2 years of age and older | brush teeth thoroughly, preferably after each meal or at least twice a day, or as directed by a dentist or physician
children 2 to 6 years | use only a pea sized amount and supervise child's brushing and rinsing (to minimize swallowing)
children under 2 years | ask a dentist or physician

Inactive ingredients

sorbitol, water, hydrated silica, PEG-12, cellulose gum, sodium lauryl sulfate, flavor, sodium saccharin, titanium dioxide, FD&C blue no. 1, D&C yellow no. 10

Questions?

1-800-468-6502

Dist. by:
COLGATE-PALMOLIVE COMPANY
New York, NY 10022

PRINCIPAL DISPLAY PANEL - 130 g Tube Label

Colgate®
Anticavity Fluoride Toothpaste

cavity
protection

Bubble Fruit®

MINECRAFT

Recyclable
Tube

ADA
Accepted
American
Dental
Association ®

NET WT 4.6 OZ (130 g)